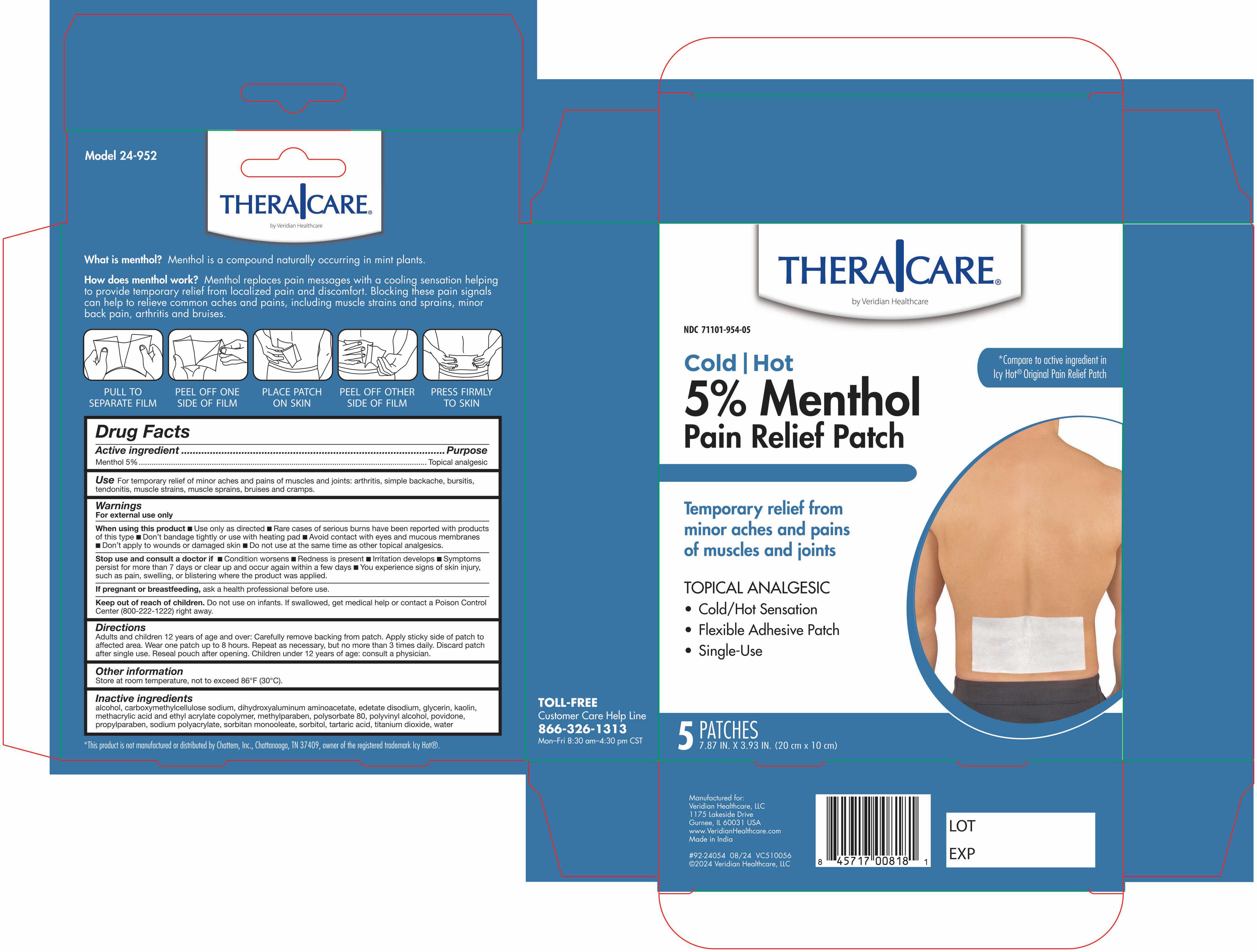 DRUG LABEL: Thera Care Cold Hot Medicated Patch
NDC: 71101-954 | Form: PATCH
Manufacturer: Veridian Healthcare
Category: otc | Type: HUMAN OTC DRUG LABEL
Date: 20240829

ACTIVE INGREDIENTS: MENTHOL 5 g/100 g
INACTIVE INGREDIENTS: SORBITAN MONOOLEATE; CARBOXYMETHYLCELLULOSE; DIHYDROXYALUMINUM AMINOACETATE; GLYCERIN; KAOLIN; METHYLPARABEN; SODIUM POLYACRYLATE (2500000 MW); POLYSORBATE 80; PROPYLPARABEN; POVIDONE, UNSPECIFIED; TARTARIC ACID; TITANIUM DIOXIDE; WATER; POLYVINYL ALCOHOL (100000 MW); ALCOHOL; METHACRYLIC ACID AND ETHYL ACRYLATE COPOLYMER; EDETATE DISODIUM; SORBITOL

Thera Care Cold Hot Medicated Patch

ACTIVE INGREDIENT

Active Ingredient ...............................................................................................Purpose
Menthol 5%...............................................................................................Topical Analgesic

PURPOSE

Topical Analgesic

INDICATIONS & USAGE

Temporarily relieves minor aches and pains of muscles and joints: ■ arthritis ■ simple backache ■ bursitis ■ tendonitis
■ muscle strains ■ muscle sprains ■ bruises ■ cramps

WARNINGS

For External Use Only.

When using this product

Use only as directed

■ Rare cases of serious burns have been reported with products of this type

■ Don’t bandage tightly or use with a heating pad
■ Avoid contact with eyes and mucous membranes ■ Don’t apply to wounds or damaged skin.■ Do not use at the same time as other topical analgesics.

Stop use and ask a doctor

If condition worsens ■ redness is present ■ If irritation develops ■symptoms persist for more than 7 days or clear up and occur again within a few days.■ You experience signs of skin injury, such as pain, swelling, or blistering where the product was applied.

If pregnant or breastfeeding

ask a health professional before use.

KEEP OUT OF REACH OF CHILDREN

Do not use in infants. If swallowed, get medical help or contact a Poison Control Center (800-222-1222) right away

DOSAGE & ADMINISTRATION

Adults and children over 12 years: Carefully remove backing from patch. Apply sticky side of patch to affected area.

Wear one patch up to 8 hours. Repeat as necessary, but no more than 3 times daily. Discard patch after single use. Reseal pouch after opening. Children under 12 years of age: Consult a physician.

Other Information

Store at room temperature, not to exceed 86F (30C)

INACTIVE INGREDIENT

Inactive ingredients

alcohol, carboxymethylcellulose sodium, dihydroxyaluminum aminoacetate, edetate disodium, glycerin, kaolin, methacrylic ac d and ethyl acrylate copolymer, methylparaben, polysorbate 80, polyvinyl alcohol, povidone, propylparaben, sodium polyacrylate, sorb tan monooleate, sorb tol, tartaric acid, titanium dioxide, water